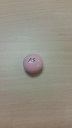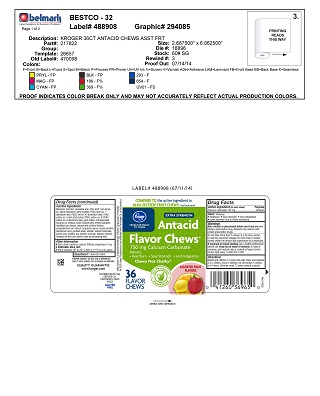 DRUG LABEL: Assort Fruit Panned
NDC: 30142-030 | Form: TABLET, CHEWABLE
Manufacturer: Kroger
Category: otc | Type: HUMAN OTC DRUG LABEL
Date: 20160216

ACTIVE INGREDIENTS: CALCIUM CARBONATE 750 mg/1 1
INACTIVE INGREDIENTS: CARNAUBA WAX

Calcium Carbonate 750mg

ACTIVE INGREDIENT

Calcium Carbonate 750mg

Purpose

Antacid

INDICATIONS AND USAGE

Uses: Relieves

- Heartburn
- Sour Stomach
- Acid Indigestion
- Upset stomach due to these symptoms

Warnings

Do not take more than 5 chews in a 24-hour period, or use the maximum dosage for more than 2 weeks, except under the advice and supervision of a physician.

Ask a doctor or pharmacist before use if you are now taking a prescription drug. Antacids may interact with certain prescription drugs.

PREGNANCY OR BREAST FEEDING

If pregnant or breast-feeding, ask a health professional before use.

Keep out of reach of children. In case of overdose, get medical help or contact a Poison Control Center right away. (1-800-222-1222)

Directions

Adults and chldren 12 years and older chew and swallow 2 to 4 chews hourly if needed. Do not exceed 5 chews in 24 hours. Children under 12 years consult a doctor.

Other information

Each chew contains: calcium 300mg, mangnesium 1mg

Contains: Soy

Store between 20C to 25C (68 to 77F) in a dry place

Inactive Ingredients:

Beeswax, carmine, carnauba wax, citric acid, corn syrup, DL-alpha tocopherol, ethyl acetate, FD&C blue #1 aluminum lake, FD&C red #40 aluminum lake, FD&C yellow #5 lake (tartrazine), FD&C yellow #6, FD&C yellow #6 aluminum lake, gum arabic, hydrogenated coconut oil, medium chain triglycerides, methly paraben, modified corn starch, natural and artificial flavors, pregelatinized corn starch, propylene glycol, propyl paraben, phosphoric acid, purified water, shellac, sodium benzoate, sorbic acid, sorbitol, soy lecithin, sucrose, titanium dioxide

Soybean oil and corn starch used as processing aids.

Questions?

1-800-632-6900